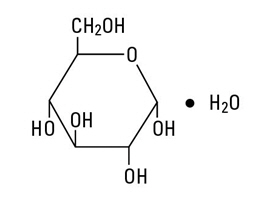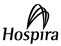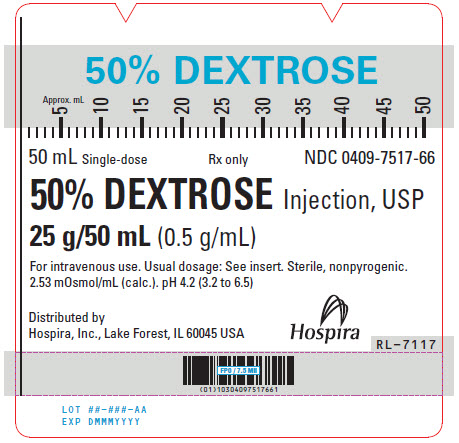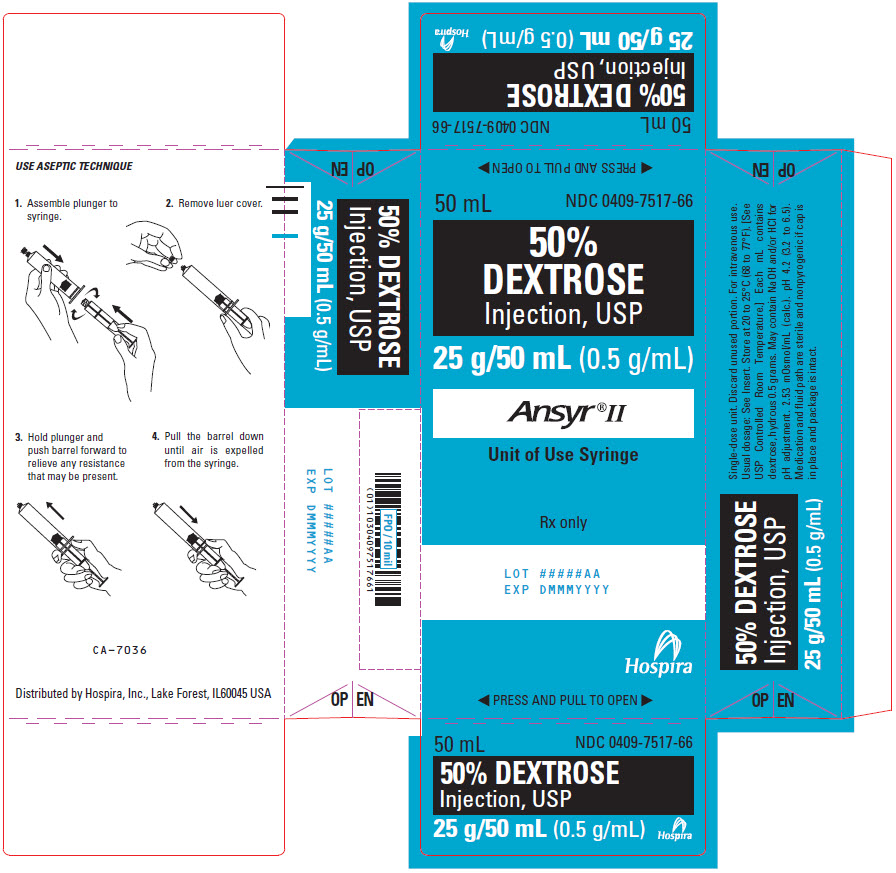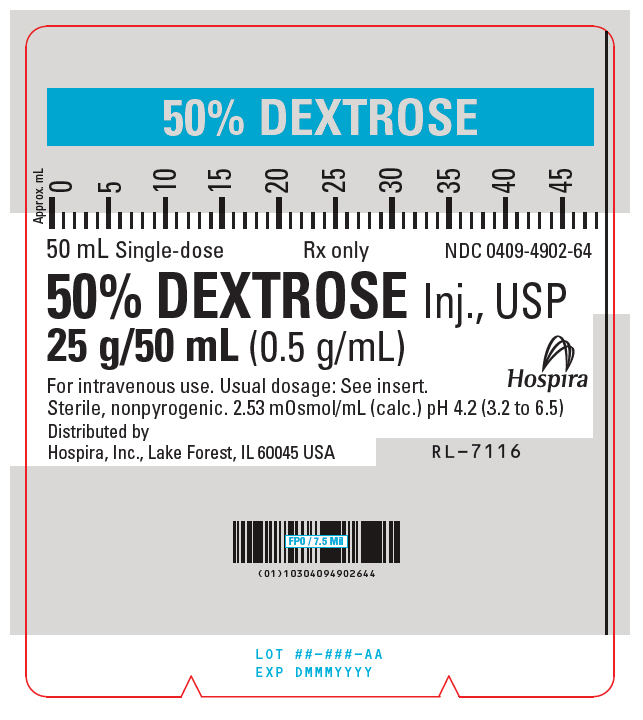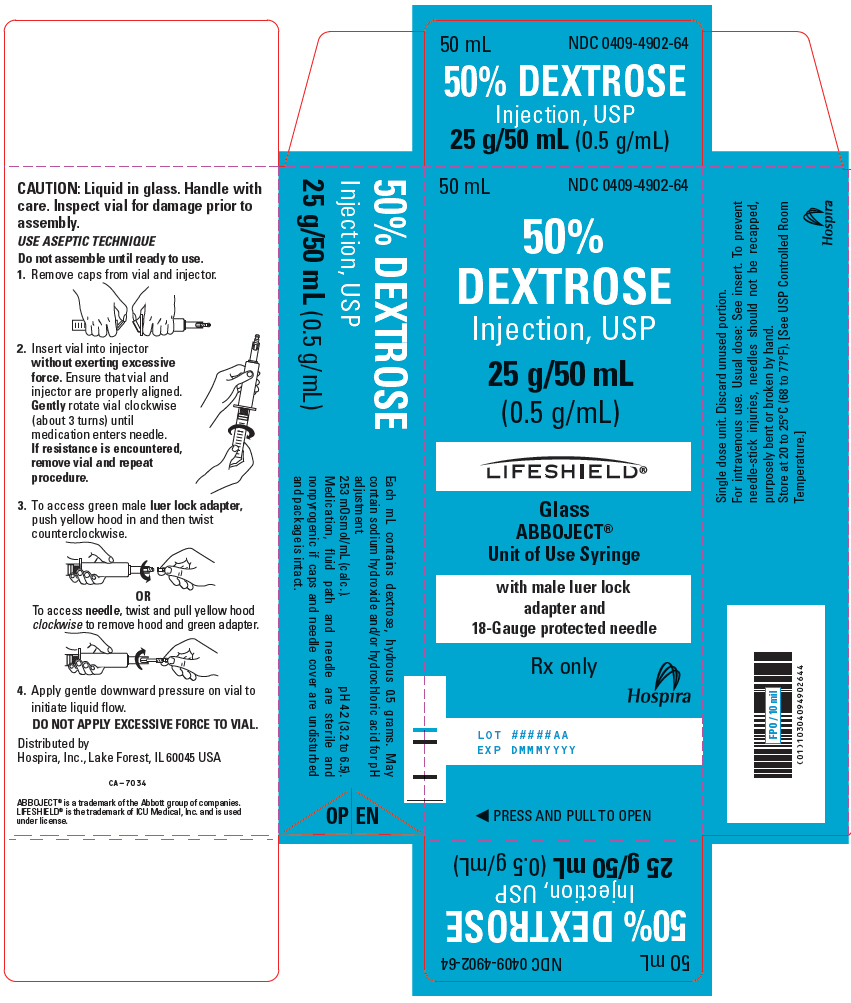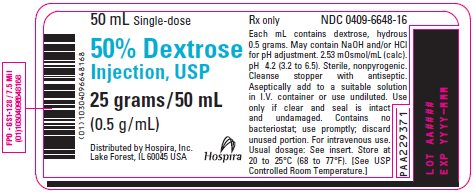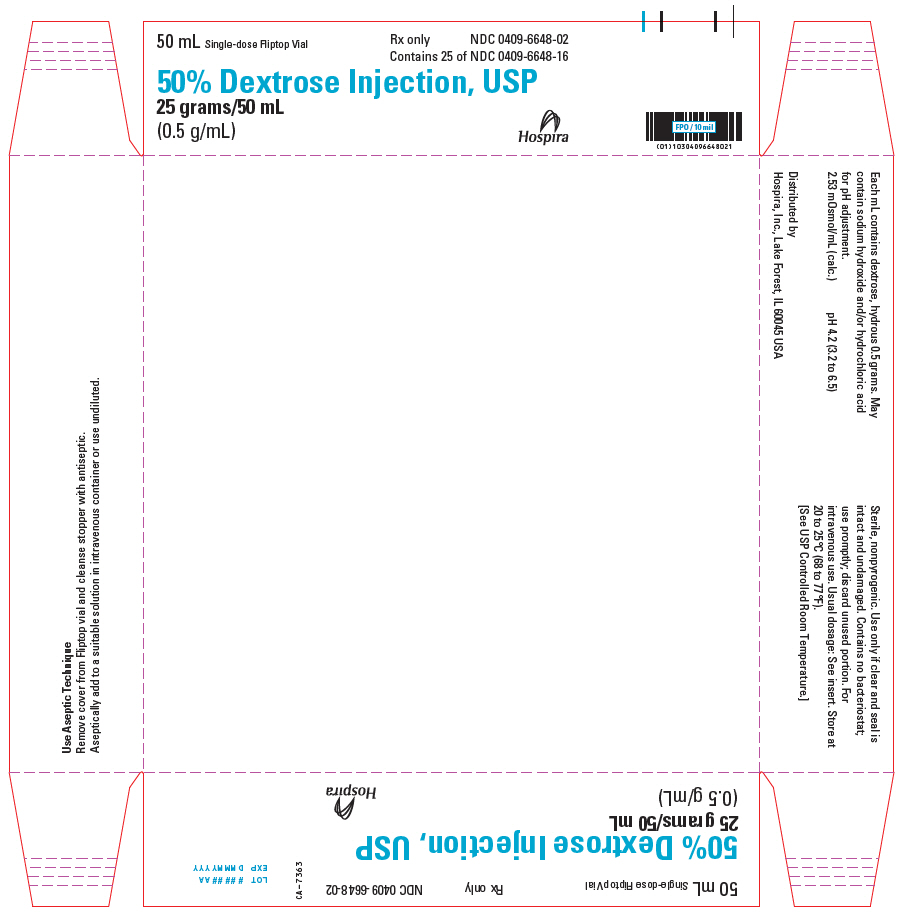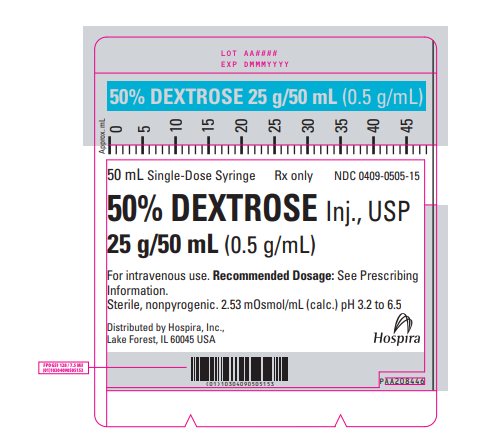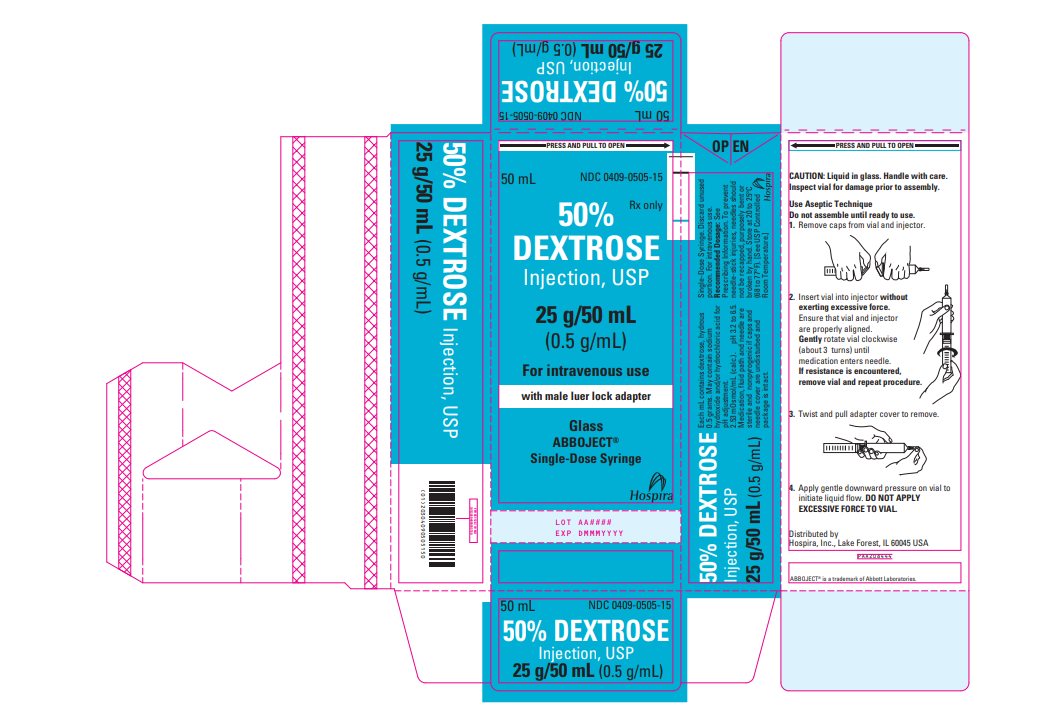 DRUG LABEL: Dextrose
NDC: 0409-7517 | Form: INJECTION, SOLUTION
Manufacturer: Hospira, Inc.
Category: prescription | Type: HUMAN PRESCRIPTION DRUG LABEL
Date: 20260127

ACTIVE INGREDIENTS: DEXTROSE MONOHYDRATE 25 g/50 mL
INACTIVE INGREDIENTS: WATER; SODIUM HYDROXIDE; HYDROCHLORIC ACID

HIGHLIGHTS OF PRESCRIBING INFORMATION

These highlights do not include all the information needed to use DEXTROSE INJECTION (50%) safely and effectively. See full prescribing information for DEXTROSE INJECTION (50%).
DEXTROSE injection, for intravenous use
Initial U.S. Approval: 1940

RECENT MAJOR CHANGES

Dosage and Administration (2.2) | 07/2025
Contraindications (4) | 07/2025
Warnings and Precautions (5.1, 5.2, 5.3, 5.4, 5.5, 5.6) | 07/2025

1 INDICATIONS AND USAGE

Dextrose Injection (50%) is indicated for the treatment of insulin-induced hypoglycemia (e.g., hyperinsulinemia, insulin shock) in adults and pediatric patients 2 years of age and older. (1)

2 DOSAGE AND ADMINISTRATION

- Only for intravenous infusion. Do not administer subcutaneously or intramuscularly. (2.1)
- Adults and Pediatric Patients 12 Years of Age and Older
  - Administer into a central vein or large peripheral vein.
  - Recommended dosage is 10 to 25 grams (20 to 50 mL) administered once. Repeated doses may be administered as clinically appropriate. (2.2)
- Pediatric Patients 2 to 11 Years of Age
  - Administer into a central vein.
  - Appropriate dosage depends on the age, weight, clinical and metabolic conditions of the patient, and concomitant therapy. (2.2)
- Maximum rate of dextrose administration without producing hyperglycemia is 0.5 g/kg of body weight/hour. (2.2)
- See full prescribing information for more information on preparation and administration instructions. (2.1, 2.2)

3 DOSAGE FORMS AND STRENGTHS

Injection: 50% (25 g/50 mL) (500 mg/mL) of single-dose dextrose hydrous supplied as:

- Ansyr® II Plastic Syringe with syringe and barrel detached
- Fliptop Vials

4 CONTRAINDICATIONS

- Intracranial or intraspinal hemorrhage. (4)
- Severe dehydration. (4)
- Alcohol withdrawal. (4)
- Known hypersensitivity to dextrose. (4)

5 WARNINGS AND PRECAUTIONS

- Hyperglycemia or Hyperosmolar Syndrome: Monitor blood and urine glucose; administer insulin as needed. (5.1)
- Hypersensitivity Reactions: Monitor for signs and symptoms and discontinue infusion immediately if reaction occurs. (5.2)
- Phlebitis and Thrombosis: Remove catheter as soon as possible if thrombophlebitis develops. (2.1, 5.3)
- Electrolyte Imbalance and Fluid Overload: Monitor changes in fluid balance, electrolyte concentrations, and acid-base balance during administration. (5.4)
- Hyponatremia: Monitor serum sodium and chloride concentrations, fluid status, acid-base balance, and neurologic status. (5.5)
- Potential Aluminum Toxicity for Patients with Immature or Impaired Renal Function: Prolonged administration of Dextrose Injection (50%) may lead to toxic levels of aluminum in pediatric patients with immature renal function or renal impairment, and in adults with renal impairment. (5.6)

6 ADVERSE REACTIONS

The most common adverse reactions are hyperglycemia, hypersensitivity reactions, hyponatremia, infection (both systemic and at the injection site), vein thrombosis, phlebitis, and electrolyte imbalance. (6)

To report SUSPECTED ADVERSE REACTIONS, contact Pfizer, Inc. at 1-800-438-1985 or FDA at 1-800-FDA-1088 or www.fda.gov/medwatch.

7 DRUG INTERACTIONS

Effects on Glycemic Control and Electrolyte Balance: Monitor blood glucose concentrations, fluid balance, serum electrolyte concentrations, and acid-base balance. Avoid use of Dextrose Injection in patients receiving drugs associated with hyponatremia. (7.1)

8 USE IN SPECIFIC POPULATIONS

Pediatric Use: Increased risk of hypoglycemia/hyperglycemia and imbalances in fluid/electrolytes; monitor serum glucose concentrations, volume status, and electrolytes. Use a different dextrose product if treatment is necessary in a pediatric patient younger than 2 years old. (8.4)

FULL PRESCRIBING INFORMATION

1 INDICATIONS AND USAGE

Dextrose (50%) Injection is indicated for the treatment of insulin-induced hypoglycemia (e.g., hyperinsulinemia, insulin shock) in adults and pediatric patients 2 years of age and older.

2 DOSAGE AND ADMINISTRATION

2.1 Important Preparation and Administration Instructions

- Parenteral drug products should be inspected visually for particulate matter and discoloration prior to administration. Do not use Dextrose Injection (50%) if the solution is cloudy or the seal has been broken.
- Obtain a blood glucose level prior to administering Dextrose Injection (50%). However, in an emergency, administer Dextrose Injection (50%) promptly without awaiting blood glucose test results.
- Do not administer Dextrose Injection (50%) simultaneously with blood through the same infusion set because pseudoagglutination of red blood cells may occur.
- Administer Dextrose Injection (50%) intravenously. Do not administer Dextrose Injection (50%) subcutaneously or intramuscularly.
- Discard the unused portion.

2.2 Recommended Dosage and Administration

Adults and Pediatric Patients 12 Years of Age and Older

When possible, administer Dextrose Injection (50%) into a central vein or large peripheral vein because Dextrose Injection (50%) has an osmolarity greater than 900 mOsm/L and can cause venous irritation.

The recommended dosage of Dextrose Injection (50%) is 10 to 25 grams (20 to 50 mL) of Dextrose Injection (50%), administered once via intravenous infusion. Repeated doses may be administered as clinically appropriate.

Slowly infuse Dextrose Injection (50%) to reduce the risk of developing hyperglycemia and to minimize venous irritation [see Warnings and Precautions (5.1, 5.3)]. The maximum rate at which Dextrose Injection (50%) can be infused without producing hyperglycemia is 0.5 g/kg of body weight/hour.

Pediatric Patients 2 to 11 Years of Age

Administer Dextrose Injection (50%) into a central vein. Avoid administration of Dextrose Injection (50%) into a peripheral vein because Dextrose Injection (50%) has an osmolarity greater than 900 mOsm/L and can cause venous irritation [Warnings and Precautions (5.3)]. If central venous access cannot be obtained, consider using an alternative commercially available dextrose product with a lower concentration.

The appropriate dosage of Dextrose Injection (50%) depends on the age, weight, clinical and metabolic conditions of the patient, and concomitant therapy.

Slowly infuse Dextrose Injection (50%) to reduce the risk of developing hyperglycemia and to minimize venous irritation [see Warnings and Precautions (5.1, 5.3)]. The maximum rate at which Dextrose Injection (50%) can be infused without producing hyperglycemia is 0.5 g/kg of body weight/hour.

3 DOSAGE FORMS AND STRENGTHS

Injection: 50% (25 g/50 mL) (500 mg/mL) of dextrose hydrous in a clear, colorless solution supplied as:

- Single-dose Ansyr® II Plastic Syringe with syringe and barrel detached
- Single-dose Fliptop Vials

4 CONTRAINDICATIONS

Dextrose Injection (50%) is contraindicated in patients with:

- Intracranial or intraspinal hemorrhage because Dextrose Injection (50%) can worsen cerebral edema by causing a fluid shift across the blood-brain barrier.
- Severe dehydration because of the potential to worsen the patient’s hyperosmolar state.
- Alcohol withdrawal because of the potential to precipitate Wernicke encephalopathy (WE) or cardiomyopathy in thiamine-deficient patients.
- Known hypersensitivity to dextrose [see Warnings and Precautions (5.2)].

5 WARNINGS AND PRECAUTIONS

5.1 Hyperglycemia and Hyperosmolar Hyperglycemic State

Significant hyperglycemia and hyperosmolar hyperglycemic state may result from too rapid administration of Dextrose Injection (50%). Symptoms of hyperosmolar hyperglycemic state include mental confusion and loss of consciousness. To minimize these risks, slowly infuse Dextrose Injection (50%) and monitor blood and urine glucose during treatment with Dextrose Injection (50%).

If Dextrose Injection (50%) is abruptly discontinued, patients should receive 5% or 10% dextrose injection to avoid rebound hypoglycemia.

5.2 Hypersensitivity Reactions

Hypersensitivity reactions, including anaphylaxis, have been reported with Dextrose Injection (50%) administration [see Adverse Reactions (6)]. Stop administration of Dextrose Injection (50%) immediately if signs or symptoms of a hypersensitivity reaction develop. Initiate appropriate treatment as clinically indicated.

5.3 Phlebitis and Thrombosis

Dextrose Injection (50%) is hypertonic (has an osmolarity greater than 900 mOsm/L) and may cause phlebitis and thrombosis at the site of injection. If thrombophlebitis occurs, remove the catheter as soon as possible.

Administer Dextrose Injection (50%) via slow intravenous infusion into a central vein (when possible) to reduce the risk of phlebitis and thrombosis. Ensure that the needle is well within the lumen of the vein and that extravasation does not occur. If thrombosis occurs, stop administration of Dextrose Injection (50%) and initiate corrective measures. Avoid administration of Dextrose Injection (50%) into a peripheral vein in pediatric patients 2 to 11 years old. If central venous access cannot be obtained in these pediatric patients, consider using an alternative commercially available dextrose product with a lower concentration.

Do not administer Dextrose Injection (50%) subcutaneously or intramuscularly.

5.4 Electrolyte Imbalance and Fluid Overload

Electrolyte deficits, particularly serum potassium and phosphate, may occur during prolonged use of Dextrose Injection (50%).

Depending on the administered volume and the infusion rate, administration of Dextrose Injection (50%) can cause fluid overload including pulmonary edema.

Avoid Dextrose Injection (50%) in patients at risk for fluid and/or solute overload. If use cannot be avoided in these patients, monitor fluid balance, electrolyte concentrations, and acid base balance, especially during prolonged use. Additional monitoring is recommended for patients with water and electrolyte disturbances that could be aggravated by increased glucose, insulin administration, and/or free water load.

5.5 Hyponatremia

Dextrose Injection (50%) may cause hyponatremia. Hyponatremia can lead to acute hyponatremic encephalopathy characterized by headache, nausea, seizures, lethargy and vomiting. The risk of hospital-acquired hyponatremia is increased in pediatric patients, geriatric patients, patients treated with diuretics, and patients with cardiac or pulmonary failure or with the syndrome of inappropriate antidiuretic hormone (SIADH) (e.g., postoperative patients, patients concomitantly treated with arginine vasopressin analogs or certain antiepileptic, psychotropic, and cytotoxic drugs) [see Drug Interactions (7.1) and Use in Specific Populations (8.4)].

Avoid Dextrose Injection (50%) in patients with or at risk for hyponatremia. If use cannot be avoided, closely monitor serum sodium concentrations, chloride concentrations, fluid status, acid-base balance, and neurologic status [see Warnings and Precautions (5.4)].

5.6 Potential Aluminum Toxicity for Patients with Immature or Impaired Renal Function

Dextrose Injection (50%) contains up to 600 mcg/L of aluminum. Prolonged administration of Dextrose Injection (50%) may lead to toxic levels of aluminum in pediatric patients with immature renal function. Due to the potential for excessive aluminum exposure, Dextrose Injection (50%) is not approved for pediatric patients younger than 2 years of age. Parenteral aluminum exposure greater than 4 to 5 mcg/kg/day has been associated with central nervous system and bone toxicity in this age group.

Prolonged administration of Dextrose Injection (50%) may also lead to toxic levels of aluminum in adults and pediatric patients with renal impairment.

6 ADVERSE REACTIONS

The following clinically significant adverse reactions are also described elsewhere in the labeling:

- Hyperglycemia and Hyperosmolar Syndrome [see Warnings and Precautions (5.1)]
- Hypersensitivity Reactions [see Warnings and Precautions (5.2)]
- Phlebitis and Thrombosis [see Warnings and Precautions (5.3)]
- Electrolyte Imbalance and Fluid Overload [see Warnings and Precautions (5.4)]
- Hyponatremia [see Warnings and Precautions (5.5)]

The following adverse reactions associated with the use of Dextrose Injection were identified in clinical trials or postmarketing reports. Because some of these reactions were reported voluntarily from a population of uncertain size, it is not always possible to reliably estimate their frequency or establish a causal relationship to drug exposure.

Administration site conditions: blister, extravasation, phlebitis, erythema, pain, vein damage, thrombosis

Immune system disorders: anaphylaxis, angioedema, bronchospasm, chills, hypotension, pruritis, pyrexia, rash

Cardiovascular disorders: cyanosis, volume overload

7 DRUG INTERACTIONS

7.1 Drugs with Effects on Glycemic Control and Electrolyte Balance

Dextrose Injection (50%) can affect glycemic control, vasopressin, and fluid and/or electrolyte balance [see Warnings and Precautions (5.1, 5.4, 5.5)]. Monitor patients’ blood glucose concentrations, fluid balance, serum electrolyte concentrations, and acid-base balance.

Concomitant administration of Dextrose Injection (50%) with drugs associated with hyponatremia may increase the risk of developing hyponatremia. Drugs associated with hyponatremia include diuretics and those that cause SIADH (e.g., selective serotonin reuptake inhibitors (SSRIs), serotonin and norepinephrine reuptake inhibitors (SNRIs), arginine vasopressin analogs, certain antiepileptic, psychotropic, and cytotoxic drugs). Avoid use of Dextrose Injection (50%) in patients receiving drugs associated with hyponatremia. If use cannot be avoided, closely monitor serum sodium concentrations during concomitant use [see Warnings and Precautions (5.5)].

8 USE IN SPECIFIC POPULATIONS

8.1 Pregnancy

Risk Summary

Appropriate administration of Dextrose Injection (50%) during pregnancy is not expected to cause adverse developmental outcomes, including congenital malformations. However, maternal hyperglycemia secondary to infusion of glucose-containing products at the time of delivery has been associated with adverse neonatal outcomes such as neonatal hypoglycemia. Animal reproduction studies have not been conducted with dextrose.

The background risk of major birth defects and miscarriage in patients with insulin-induced hypoglycemia (e.g., hyperinsulinemia, insulin shock) is unknown. All pregnancies have a background risk of birth defect, loss, or other adverse outcomes. In the U.S. general population, the estimated background risk of major birth defects and miscarriage in clinically recognized pregnancies is 2 to 4% and 15 to 20%, respectively.

8.2 Lactation

Risk Summary

There are no data on the effects of Dextrose Injection (50%) on levels of glucose in human milk, on the breastfed infant, or on milk production. The developmental and health benefits of breastfeeding should be considered along with the mother’s clinical need for Dextrose Injection (50%) and any potential adverse effects on the breastfed infant from Dextrose Injection (50%) or from the underlying maternal condition.

8.4 Pediatric Use

Dextrose Injection (50%) is indicated in pediatric patients aged 2 years and older for the treatment of insulin-induced hypoglycemia (e.g., hyperinsulinemia, or insulin shock).

Monitor plasma electrolyte concentrations closely in pediatric patients who may have impaired ability to regulate fluids and electrolytes [see Warnings and Precautions (5.4)]. Pediatric patients treated with Dextrose Injection (50%) are at increased risk of developing hyponatremia and hyponatremic encephalopathy [see Warnings and Precautions (5.5)].

Dextrose Injection (50%) is not indicated for use in neonates. Dextrose Injection (50%) can increase the risk of developing hypo- or hyperglycemia in neonates, especially preterm neonates with low birth weight. Excessive or rapid administration of Dextrose Injection (50%) may also result in increased serum osmolality and risk of intracerebral hemorrhage in very low birth weight neonates.

Dextrose Injection (50%) is not indicated for use in pediatric patients younger than 2 years old due to the potential for excessive aluminum exposure. If treatment with Dextrose Injection (50%) is necessary in a pediatric patient younger than 2 years old, use a different dextrose product [see Indications and Usage (1) and Warnings and Precautions (5.6)].

8.5 Geriatric Use

Dextrose Injection (50%) has not been studied in a sufficient number of patients aged 65 and over to determine whether they respond differently from younger adult patients. Geriatric patients are at increased risk of developing hyponatremia and hyponatremic encephalopathy [see Warnings and Precautions (5.5)]. Other reported clinical experience has not identified differences in responses between the geriatric and younger adult patients. In general, the infusion rate for geriatric patients should start low and be titrated up cautiously, reflecting the greater risk for electrolyte abnormalities and fluid overload.

Dextrose is known to be substantially excreted by the kidney, and the risk of adverse reactions to Dextrose Injection (50%) may be greater in patients with impaired renal function. Because geriatric patients are more likely to have impaired renal function, care should be taken in selection of the infusion rate, and patients should be closely monitored during Dextrose Injection (50%) treatment.

10 OVERDOSAGE

A medication error resulting in a high infusion rate of Dextrose Injection (50%) can cause hyperglycemia, hyperosmolality, and adverse effects on fluid and electrolyte balance [see Warnings and Precautions (5.1, 5.4)].

Severe hyperglycemia and severe dilutional hyponatremia, and their complications, can be fatal. In the event of overdosage (overhydration or solute overload) during Dextrose Injection (50%) treatment, discontinue the infusion. Institute corrective measures such as administration of exogenous insulin, and treat adverse effects on the CNS, respiratory, and cardiovascular systems [see Warnings and Precautions (5.1, 5.4)].

11 DESCRIPTION

Dextrose, USP is chemically designated C6H12O6 • H2O (D-glucose monohydrate), a hexose sugar freely soluble in water.

Dextrose, hydrous has the following structural formula:

Water for Injection, USP is chemically designated H2O. The molecular weight of dextrose (D-glucose) monohydrate is 198.17.

Dextrose Injection, USP (50%) is a sterile, nonpyrogenic, hypertonic solution of dextrose in water for injection for intravenous injection.

Each milliliter (mL) of fluid contains 0.5 grams of dextrose, hydrous which delivers 3.4 kcal/gram (0.85 kcal/mL). The solution has an osmolarity of 2.53 mOsmol/mL (calculation) and the pH range is 3.2 to 6.5. May contain sodium hydroxide and/or hydrochloric acid for pH adjustment.

The Dextrose Injection (50%) vial contains no more than 600 mcg/L of aluminum.

The solution contains no bacteriostatic, antimicrobial agent or added buffer (except for pH adjustment) and is supplied as single-dose containers.

Dextrose is derived from corn.

12 CLINICAL PHARMACOLOGY

12.1 Mechanism of Action

Dextrose restores blood glucose levels and provides a source of carbohydrate calories.

12.2 Pharmacodynamics

The exposure-response relationship and time course of pharmacodynamic response for the safety and effectiveness of dextrose have not been fully characterized.

12.3 Pharmacokinetics

Dextrose is oxidized to carbon dioxide and water.

13 NONCLINICAL TOXICOLOGY

13.1 Carcinogenesis, Mutagenesis, Impairment of Fertility

Studies with dextrose to evaluate the drug’s carcinogenic potential, mutagenic potential, or effects on fertility have not been performed.

16 HOW SUPPLIED/STORAGE AND HANDLING

How Supplied

Dextrose Injection, USP (50%) is supplied as a clear, colorless solution in single-dose containers as follows:

Unit of Sale and Product Description | Strength; (Concentration) | NDC
Bundle of 10; 50 mL Ansyr® II Plastic Syringe with syringe and barrel detached | 50% (25 g/50 mL) (0.5 g/mL) | 0409-7517-16
Tray of 25; 50 mL Single-Dose Fliptop Vials | 50% (25 g/50 mL); (0.5 g/mL) | 0409-6648-02

Storage and Handling

Minimize exposure of Dextrose Injection (50%) to heat. Avoid excessive heat. Protect from freezing. Store at 20°C to 25°C (68°F to 77°F) [See USP Controlled Room Temperature.]

Distributed by Hospira, Inc., Lake Forest, IL 60045 USA

LAB-1027-9.0

PRINCIPAL DISPLAY PANEL - 50 mL Syringe Label - 0409-7517-66

50% DEXTROSE

50 mL Single-dose
Rx only
NDC 0409-7517-66

50% DEXTROSE Injection, USP
25 g/50 mL (0.5 g/mL)

For intravenous use. Usual dosage: See insert. Sterile, nonpyrogenic.
2.53 mOsmol/mL (calc.). pH 4.2 (3.2 to 6.5)

Distributed by
Hospira, Inc., Lake Forest, IL 60045 USA
Hospira
RL-7117

LOT ##-###-AA
EXP DMMMYYYY

PRINCIPAL DISPLAY PANEL - 50 mL Syringe Carton - 0409-7517-66

50 mL
NDC 0409-7517-66

50%
DEXTROSE
Injection, USP

25 g/50 mL (0.5 g/mL)

Ansyr®II

Unit of Use Syringe

Rx only

LOT #####AA
EXP DMMMYYYY

Hospira

◀ PRESS AND PULL TO OPEN ▶

PRINCIPAL DISPLAY PANEL - 50 mL Syringe Label - 0409-4902-64

50% DEXTROSE

50 mL Single-dose
Rx only
NDC 0409-4902-64

50% DEXTROSE Inj., USP
25 g/50 mL (0.5 g/mL)

For intravenous use. Usual dosage: See insert.
Sterile, nonpyrogenic. 2.53 mOsmol/mL (calc.) pH 4.2 (3.2 to 6.5)
Distributed by
Hospira, Inc., Lake Forest, IL 60045 USA

Hospira

RL–7116

LOT ##–###–AA

EXP DMMMYYYY

PRINCIPAL DISPLAY PANEL - 50 mL Syringe Carton - 0409-4902-64

50 mL
NDC 0409-4902-64

50%
DEXTROSE
Injection, USP

25 g/50 mL
(0.5 g/mL)

LIFESHIELD®

Glass
ABBOJECT®
Unit of Use Syringe

with male luer lock
adapter and
18-Gauge protected needle

Rx only

Hospira

LOT #####AA

EXP DMMMYYYY

◀ PRESS AND PULL TO OPEN

PRINCIPAL DISPLAY PANEL - 50 mL Vial Label - 0409-6648-16

50 mL Single-dose

50% Dextrose
Injection, USP

25 grams/50 mL
(0.5 g/mL)
Distributed by Hospira, Inc.
Lake Forest, IL 60045 USA

Hospira

PRINCIPAL DISPLAY PANEL - 50 mL Vial Tray - 0409-6648-02

50 mL Single-dose Fliptop Vial

Rx only
NDC 0409-6648-02
Contains 25 of NDC 0409-6648-16

50% Dextrose Injection, USP

25 grams/50 mL
(0.5 g/mL)

Hospira

PRINCIPAL DISPLAY PANEL - 50 mL Syringe Label - 0409-0505-15

50 mL Single-Dose Syringe

Rx only

NDC 0409-0505-15

50% DEXTROSE Inj., USP
25 g/50 mL (0.5 g/mL)

For intravenous use. Recommended Dosage: See Prescribing
Information.
Sterile, nonpyrogenic. 2.53 mOsmol/mL (calc.) pH 3.2 to 6.5

Distributed by Hospira, Inc.,
Lake Forest, IL 60045 USA

Hospira

PRINCIPAL DISPLAY PANEL - 50 mL Vial Carton - 0409-0505-15

PRESS AND PULL TO OPEN

50 mL

NDC 0409-0505-15

Rx only

50%
DEXTROSE
Injection, USP

25 g/50 mL
(0.5 g/mL)

For intravenous use

with male luer lock adapter

Glass
Abboject®
Single-Dose Syringe

Hospira